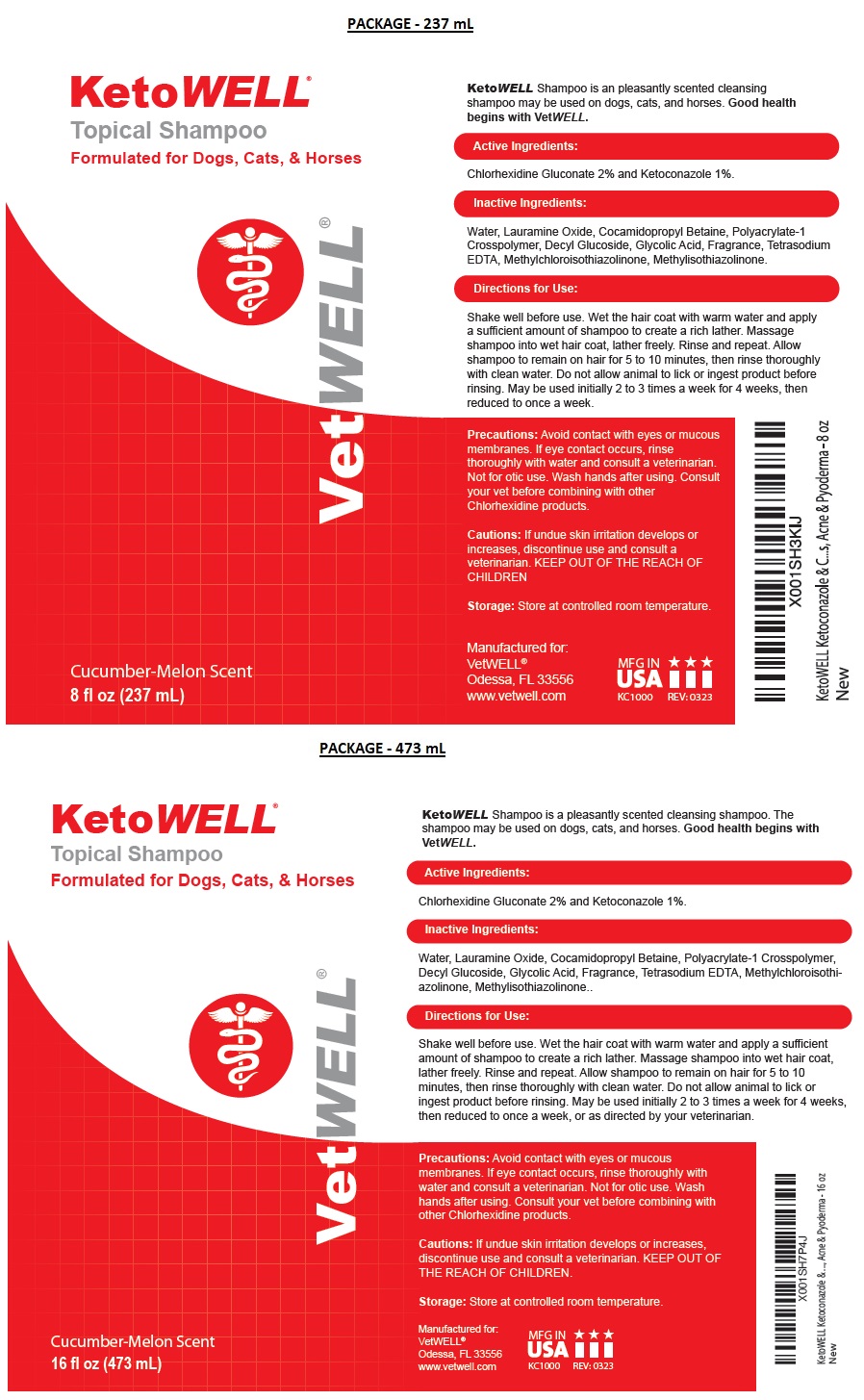 DRUG LABEL: KetoWELL
NDC: 86090-004 | Form: SHAMPOO
Manufacturer: Pet MD Brands, LLC
Category: animal | Type: OTC ANIMAL DRUG LABEL
Date: 20230907

ACTIVE INGREDIENTS: CHLORHEXIDINE GLUCONATE 2 g/100 mL; KETOCONAZOLE 1 g/100 mL
INACTIVE INGREDIENTS: WATER; LAURAMINE OXIDE; COCAMIDOPROPYL BETAINE; POLYACRYLATE-1 CROSSPOLYMER; DECYL GLUCOSIDE; GLYCOLIC ACID; EDETATE SODIUM; METHYLCHLOROISOTHIAZOLINONE; METHYLISOTHIAZOLINONE

KetoWELL® Shampoo

Active Ingredients:

Chlorhexidine Gluconate 2% and Ketoconazole 1%.

INDICATIONS AND USAGE

KetoWELL Shampoo is a pleasantly scented cleansing shampoo. The shampoo may be used on dogs, cats, and horses. Good health begins with VetWELL.

Inactive Ingredients:

Water, Lauramine Oxide, Cocamidopropyl Betaine, Polyacrylate-1 Crosspolymer, Decyl Glucoside, Glycolic Acid, Fragrance, Tetrasodium EDTA, Methylchloroisothiazolinone, Methylisothiazolinone.

Directions for Use:

Shake well before use. Wet the hair coat with warm water and apply a sufficient amount of shampoo to create a rich lather. Massage shampoo into wet hair coat, lather freely. Rinse and repeat. Allow shampoo to remain on hair for 5 to 10 minutes, then rinse thoroughly with clean water. Do not allow animal to lick or ingest product before rinsing. May be used initially 2 to 3 times a week for 4 weeks, then reduced to once a week, or as directed by your veterinarian.

Precautions:

Avoid contact with eyes or mucous membranes. If eye contact occurs, rinse thoroughly with water and consult a veterinarian. Not for otic use. Wash hands after using. Consult your vet before combining with other Chlorhexidine products.

Cautions:

If undue skin irritation develops or increases, discontinue use and consult a veterinarian. KEEP OUT OF THE REACH OF CHILDREN.

Storage:

Store at controlled room temperature.

Formulated for Dogs, Cats, & Horses

Cucumber-Melon Scent

Manufactured for:
VetWELL®
Odessa, FL 33556
www.vetwell.com

MFG IN USA